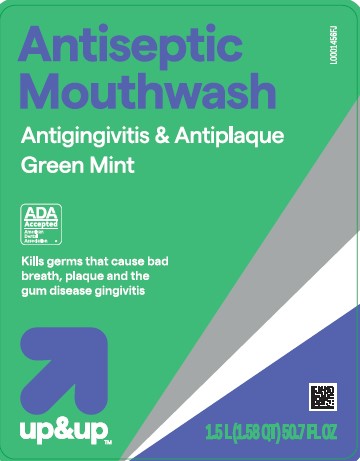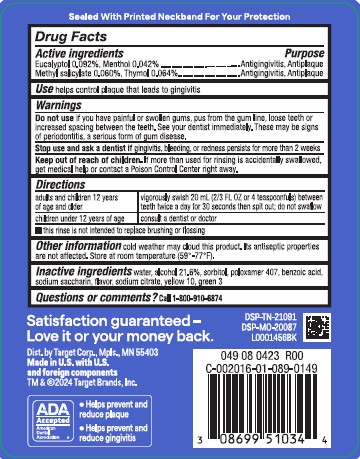 DRUG LABEL: Antispetic
NDC: 11673-072 | Form: MOUTHWASH
Manufacturer: Target Corporation
Category: otc | Type: HUMAN OTC DRUG LABEL
Date: 20260218

ACTIVE INGREDIENTS: EUCALYPTOL 0.92 mg/1 mL; MENTHOL 0.42 mg/1 mL; METHYL SALICYLATE 0.6 mg/1 mL; THYMOL 0.64 mg/1 mL
INACTIVE INGREDIENTS: WATER; ALCOHOL; SORBITOL SOLUTION; POLOXAMER 407; BENZOIC ACID; SACCHARIN SODIUM; SODIUM CITRATE; D&C YELLOW NO. 10; FD&C GREEN NO. 3

Up & Up 072.003/072AL rev2-AN
Spring Mint Antiseptic Mouthrinse

Tamper Evident Statement

Sealed With Printed Neckband For Your Protection

Active ingredients

Eucalyptol 0.092%

Menthol 0.042%

Methyl salicylate 0.060%

Thymol 0.064%

Purpose

Antigingivitis, Antiplaque

Use

helps control plaque that leads to gingivitis

Warnings

for this product

Do not use

if you have painful or swollen gums, pus from the gum line, loose teeth or increased spacing between the teeth. See your dentist immediately. These may be signs of periodontitis, a serious form of gum disease.

Stop use and ask a dentist if

gingivitis, bleeding, or redness persists for more than 2 weeks.

Keep out of reach of children.

If more than used for rinsing is accidentally swallowed, get medical help or contact a Poison Control Center right away.

Directions

adults and children 12 years of age and older - vigorously swish 20 mL (2/3 FL OZ or 4 teaspoonfuls) between teeth twice a day for 30 seconds then spit out; do not swallow

children under 12 years of age - consult a dentist or doctor

- this rinse is not intended to replace brushing or flossing

Other information

cold weather may cloud this product. Its antiseptic properties are not affected. Store at room temperature (59⁰ - 77⁰F).

Inactive ingredients

water, alcohol 21.6%, sorbitol, flavor, poloxamer 407, benzoic acid, sodium saccharin, sodium citrate, yellow 10, green 3

Questions or comments?

Call 1-800-910-6874

Adverse Reactions

Satisfaction guaranteed -

Love it or your money back.

Dist. by Target Corp., Mpls., MN 55403

Made in U.S. with U.S. and foreign components

TM & ©2024 Target Brands, Inc.

DSP-TN-21091

DSP-MO-20087

ADA Accepted

American Dental Association

- Helps prevent and reduce plaque
- Helps prevent and reduce gingivitis

Principal display panel

Antiseptic

Mouthwash

Antigingivitis & Antiplaque

Green Mint

ADA Accepted

American Dental Association

Kills germs that cause bad breath, plaque and the gum disease gingivitis

up & up™

1.5 L (1.58 QT) 50.7 FL OZ